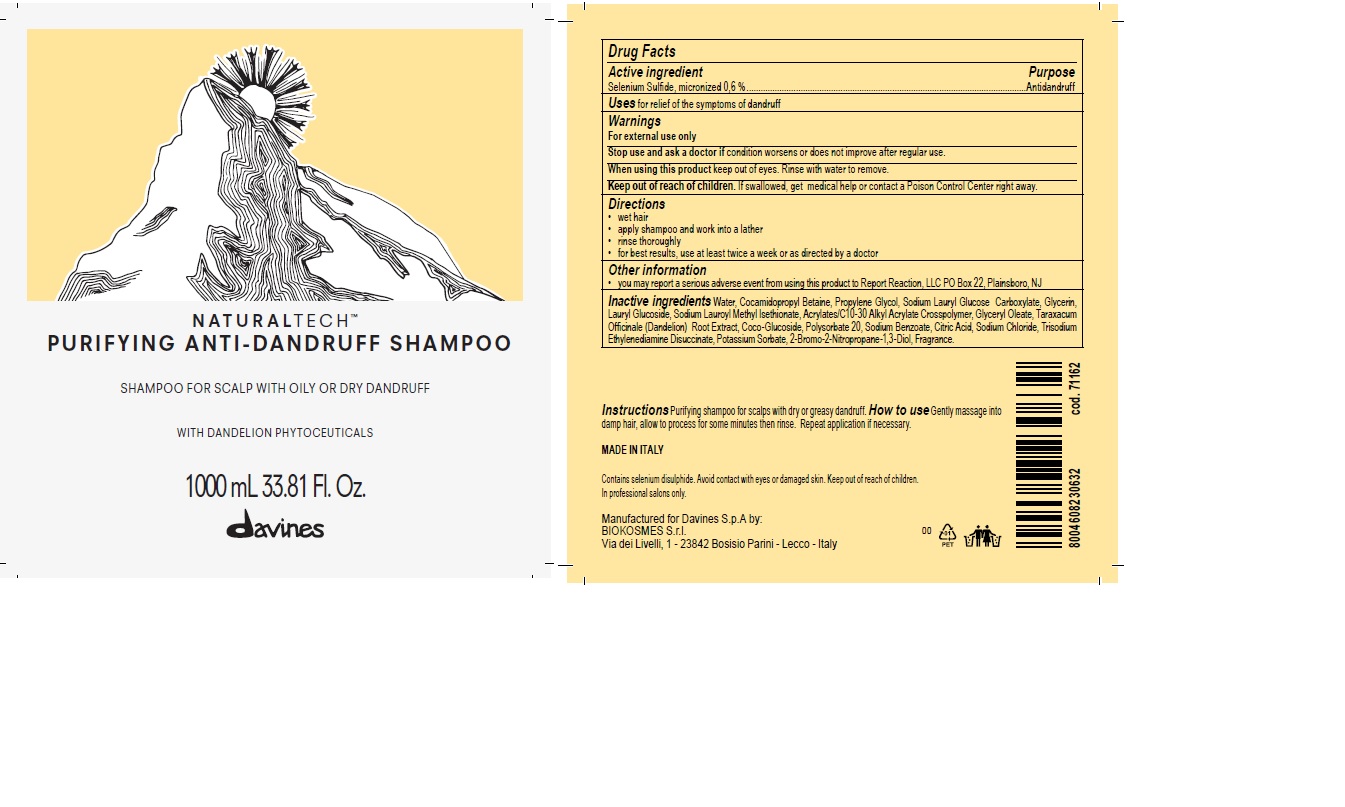 DRUG LABEL: NATURALTECH PURIFYING ANTI-DANDRUFF
NDC: 64724-1016 | Form: SHAMPOO
Manufacturer: Davines S.p.A.
Category: otc | Type: HUMAN OTC DRUG LABEL
Date: 20241211

ACTIVE INGREDIENTS: SELENIUM SULFIDE 0.6 g/100 mL
INACTIVE INGREDIENTS: WATER; COCAMIDOPROPYL BETAINE; PROPYLENE GLYCOL; GLYCERIN; LAURYL GLUCOSIDE; CARBOMER COPOLYMER TYPE A (ALLYL PENTAERYTHRITOL CROSSLINKED); GLYCERYL OLEATE; TARAXACUM OFFICINALE; COCO GLUCOSIDE; POLYSORBATE 20; SODIUM BENZOATE; CITRIC ACID MONOHYDRATE; SODIUM CHLORIDE; TRISODIUM ETHYLENEDIAMINE DISUCCINATE; POTASSIUM SORBATE; BRONOPOL; LINALOOL, (+/-)-

NATURALTECH™ PURIFYING ANTI-DANDRUFF SHAMPOO

Drug Facts

Active ingredient

Selenium Sulfide, micronized 0,6 %

Purpose

Antidandruff

Uses

for relief of the symptoms of dandruff

Warnings

For external use only

Stop use and ask a doctor if condition worsens or does not improve after regular use.

When using this product keep out of eyes. Rinse with water to remove.

Keep out of reach of children. If swallowed, get medical help or contact a Poison Control Center right away.

Directions

- wet hair
- apply shampoo and work into a lather
- rinse thoroughly
- for best results, use at least twice a week or as directed by a doctor

Other information

- you may report a serious adverse event from using this product to Report Reaction, LLC PO Box 22, Plainsboro, NJ

Inactive ingredients

Water, Cocamidopropyl Betaine, Propylene Glycol, Sodium Lauryl Glucose Carboxylate, Glycerin, Lauryl Glucoside, Sodium Lauroyl Methyl Isethionate, Acrylates/C10-30 Alkyl Acrylate Crosspolymer, Glyceryl Oleate, Taraxacum Officinale (Dandelion) Root Extract, Coco-Glucoside, Polysorbate 20, Sodium Benzoate, Citric Acid, Sodium Chloride, Trisodium Ethylenediamine Disuccinate, Potassium Sorbate, 2-Bromo-2-Nitropropane-1,3-Diol, Fragrance.

PRINCIPAL DISPLAY PANEL - 1000 mL Bottle Label

NATURALTECH™
PURIFYING ANTI-DANDRUFF SHAMPOO

SHAMPOO FOR SCALP WITH OILY OR DRY DANDRUFF

WITH DANDELION PHYTOCEUTICALS

1000 mL 33.81 Fl. Oz.

davines